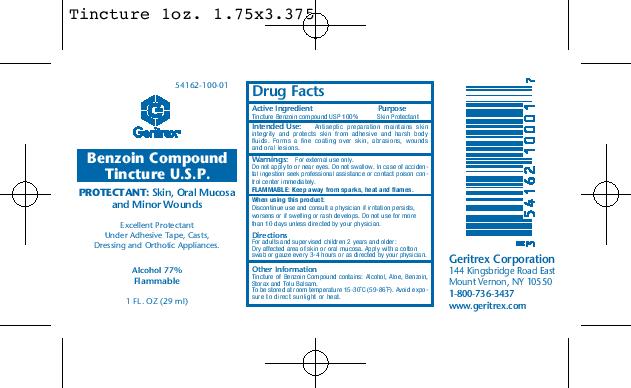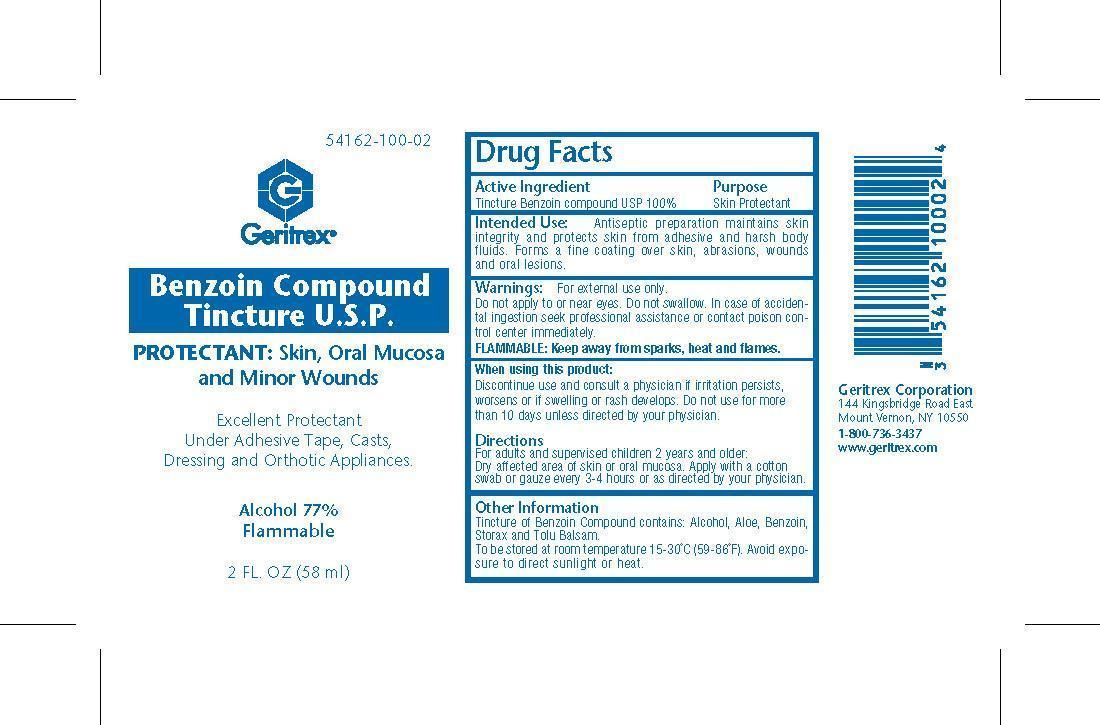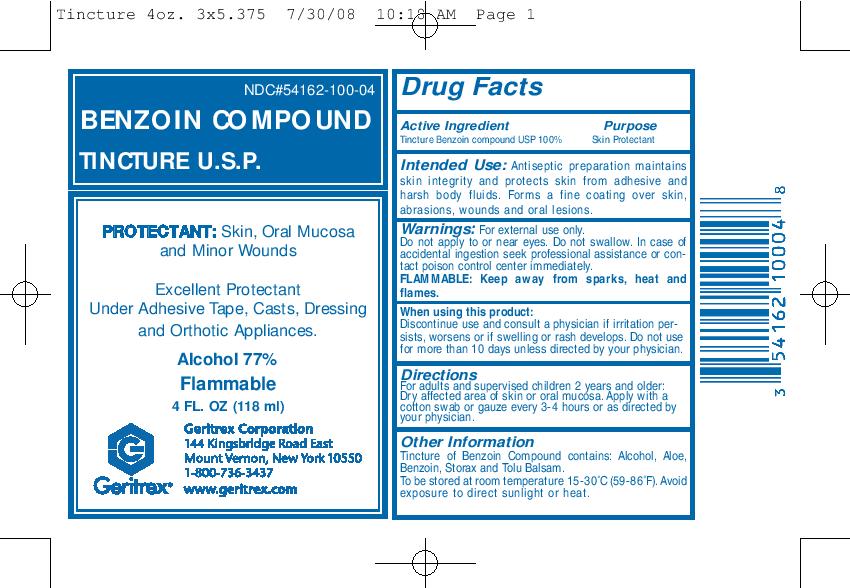 DRUG LABEL: Benzoin Compound Tincture
NDC: 54162-100 | Form: LIQUID
Manufacturer: Geritrex LLC
Category: otc | Type: HUMAN OTC DRUG LABEL
Date: 20180117

ACTIVE INGREDIENTS: BENZOIN RESIN 100 mg/1 mL
INACTIVE INGREDIENTS: ALCOHOL; ALOE; LIQUIDAMBAR ORIENTALIS RESIN; TOLU BALSAM

Benzoin Compound Tincture

Active Ingredient

Tincture Benzoin compound

Intended Use

Antiseptic preparation maintains skin
integrity and protects skin from adhesive and harsh body
fluids. Forms a fine coating over skin, abrasions, wounds
and oral lesions.

Directions

For adults and supervised children 2 years and older:
Dry affected area of skin or oral mucosa. Apply with a cotton
swab or gauze every 3-4 hours or as directed by your physician.

Warnings

For external use only.
Do not apply to or near eyes. Do not swallow. In case of accidental
ingestion seek professional assistance or contact poison control
center immediately.
FLAMMABLE: Keep away from sparks, heat and flames.
When using this product:
Discontinue use and consult a physician if irritation persists,
worsens or if swelling or rash develops. Do not use for more
than 10 days unless directed by your physician.

DOSAGE AND ADMINISTRATION

Apply with a cotton
swab or gauze every 3-4 hours

INACTIVE INGREDIENT

Benzoin Resin

STORAGE AND HANDLING

To be stored at room temperature 15-30°C (59-86°F). Avoid exposure
to direct sunlight or heat.

KEEP OUT OF REACH OF CHILDREN.